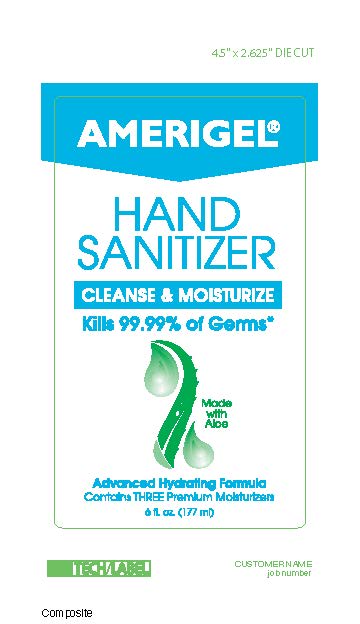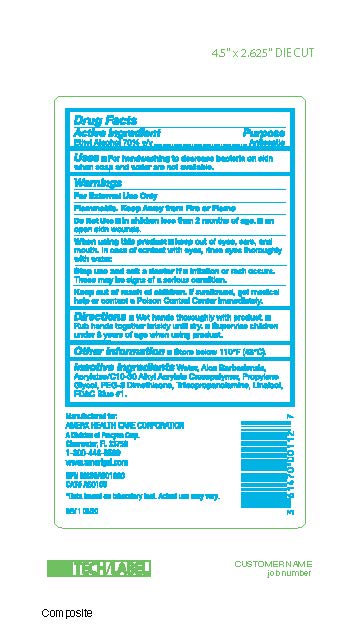 DRUG LABEL: Amerigel Hand Sanitizer
NDC: 61470-001 | Form: GEL
Manufacturer: Amerx Health Care Corp
Category: otc | Type: HUMAN OTC DRUG LABEL
Date: 20200622

ACTIVE INGREDIENTS: ALCOHOL 123.9 mL/177 mL
INACTIVE INGREDIENTS: (C10-C30)ALKYL METHACRYLATE ESTER; ALOE VERA LEAF; WATER; PEG-8 DIMETHICONE; TRIISOPROPANOLAMINE; PROPYLENE GLYCOL BUTYL ETHER; LINALOOL, (+)-

Amerigel Hand Sanitizer

Active Ingredient

Ethyl Alcohol 70%

Purpose

Antiseptic

Uses

For handwashing to decrease bacteria on skin when soap and water are not available.

Warnings

For External Use only. Flammable. Keep away from heat or flame.

Do not use

In children less than 2 months of age. On open skin wounds.

When using this product

Keep out of eyes, ears, and mouth. In case of contact with eyes, rinse eyes thoroughly with water.

Stop use and ask a doctor.

If irritation or rash occurs. These may be signs of a serious condition.

Keep out of reach of children.

If swallowed, get medical help or contact a Poison Control Center immediately.

Directions

Wet hands thoroughly with product. Rub hands together briskly until dry. Supervise children under 6 years of age when using this product.

Other Information

Store below 110F (43C)

Inactive Ingredients

Water, Aloe Barbadensis, Acrylates/C10-30 Alkyl Acrylate Crosspolymer, Propylene Glycol, PEG-8 Dimethicone, Triisopropanolamine, Linalool, FD&C Blue #1